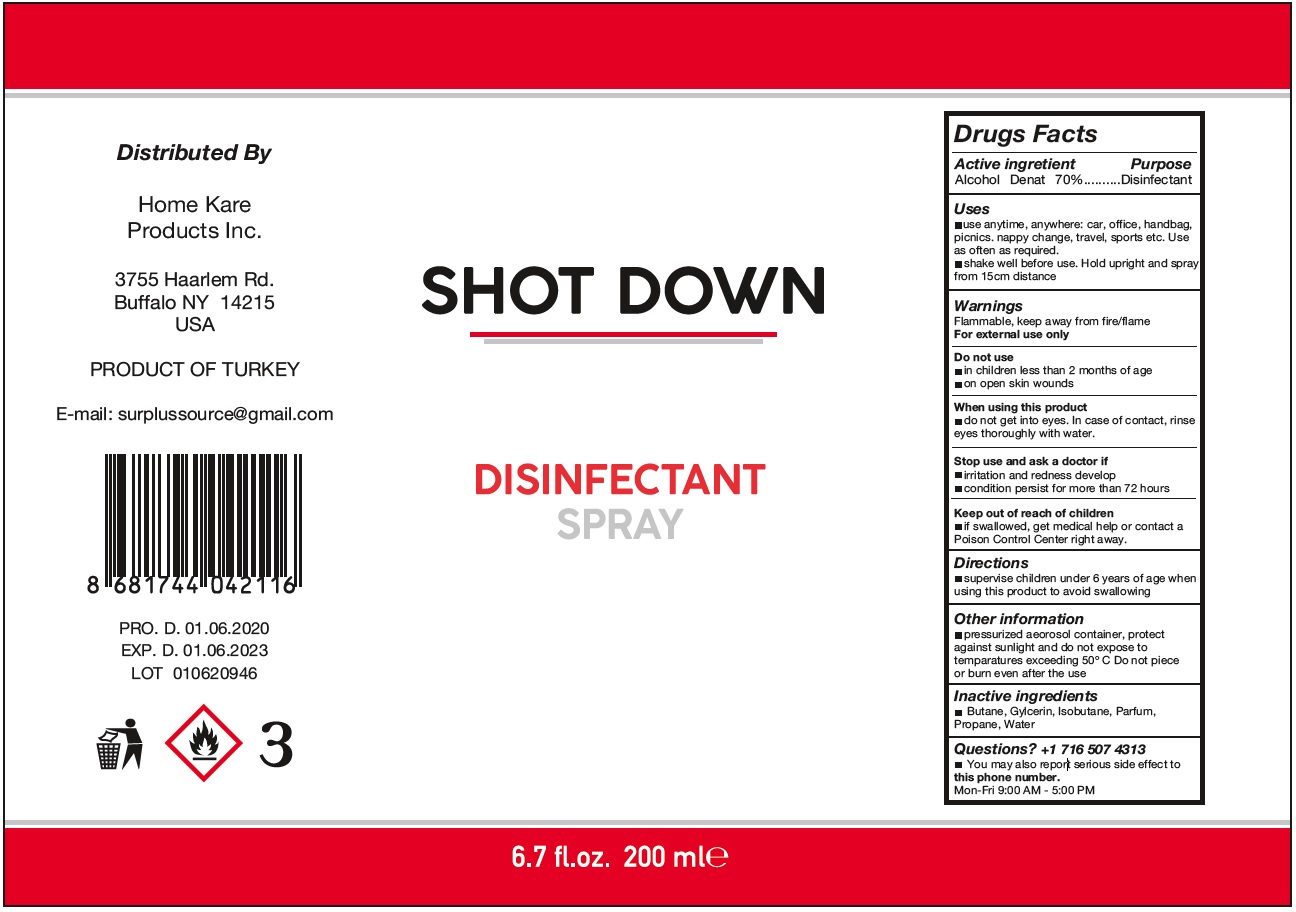 DRUG LABEL: SHOT DOWN
NDC: 81402-102 | Form: SPRAY
Manufacturer: PRIVATE LABEL AEROSOL DOLUM SANAYI TICARET ANONIM SIRKETI
Category: otc | Type: HUMAN OTC DRUG LABEL
Date: 20210113

ACTIVE INGREDIENTS: ALCOHOL 70 mL/100 mL
INACTIVE INGREDIENTS: BUTANE; GLYCERIN; ISOBUTANE; PROPANE; WATER

SHOT DOWN DISINFECTANT SPRAY

Active ingredient

Alcohol Denat 70%

Purpose

Disinfectant

Uses

• use anytime, anywhere: car, office, handbag, picnics. nappy change, travel, sports etc. Use as often as required.
• shake well before use. Hold upright and spray from 15cm distance

Warnings

Flammable, keep away from fire/flame
For external use only

Do not use

• in children less than 2 months of age
• on open skin wounds

When using this product
• do not get into eyes. In case of contact, rinse eyes thoroughly with water.

Stop use and ask a doctor if
• irritation and redness develop
• condition persist for more than 72 hours

Keep out of reach of children

• if swallowed, get medical help or contact a Poison Control Center right away.

Directions

• supervise children under 6 years of age when using this product to avoid swallowing

Other information

• pressurized aerosol container, protect against sunlight and do not expose to temperatures exceeding 50º C. Do not pierce or burn even after the use

Inactive ingredients

• Butane, Gylcerin, Isobutane, Parfum, Propane, Water

Questions? +1 716 507 4313

• You may also report serious side effect to this phone number.
Mon-Fri 9:00 AM - 5:00 PM

Distributed By

Home Kare Products Inc.

3755 Haarlem Rd.
Buffalo NY 14215
USA

PRODUCT OF TURKEY

E-mail: surplussource@gmail.com